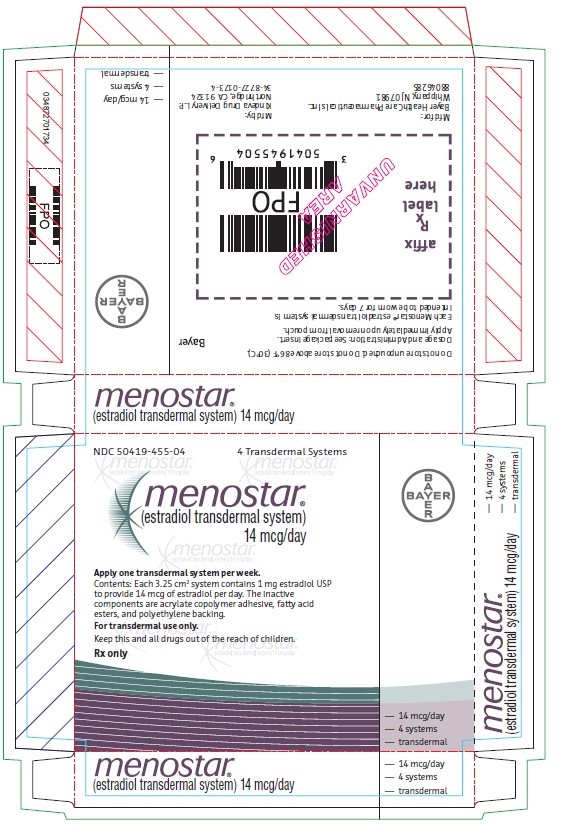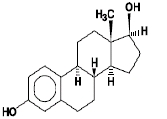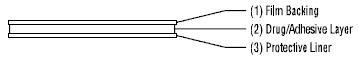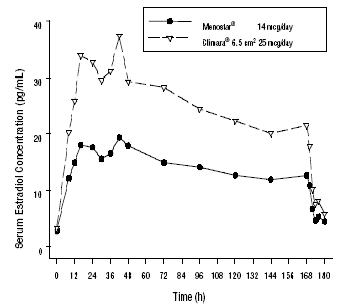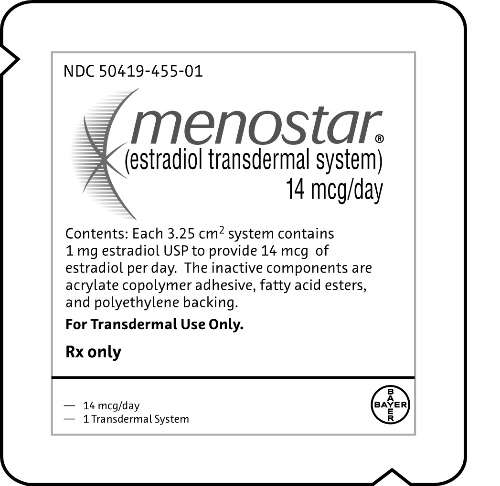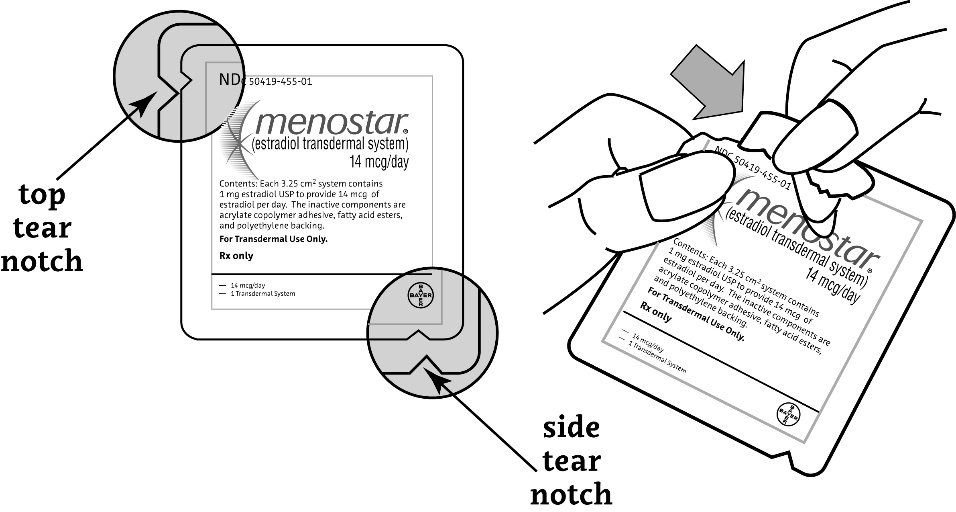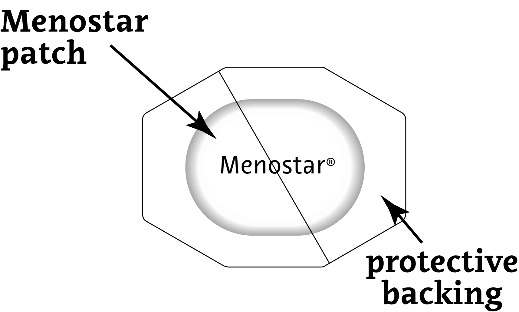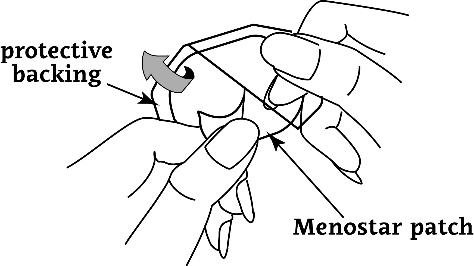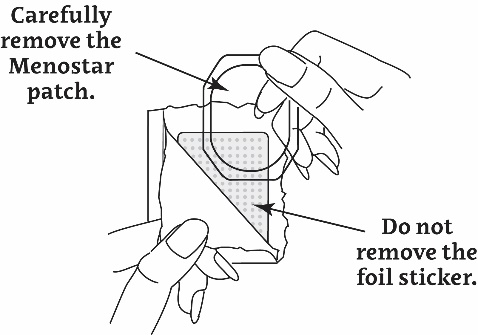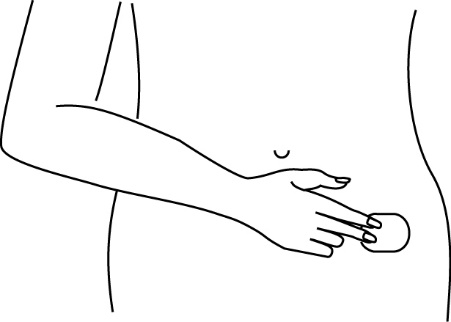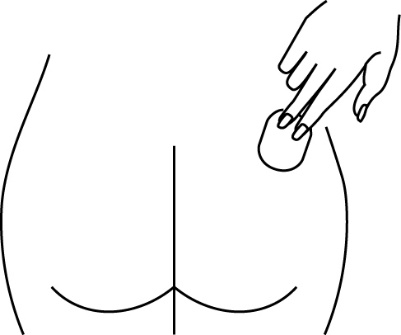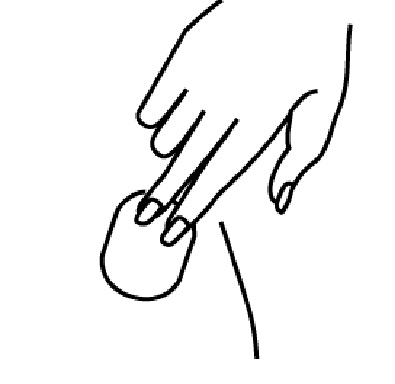 DRUG LABEL: Menostar
NDC: 50419-455 | Form: PATCH
Manufacturer: Bayer HealthCare Pharmaceuticals Inc.
Category: prescription | Type: HUMAN PRESCRIPTION DRUG LABEL
Date: 20231208

ACTIVE INGREDIENTS: ESTRADIOL 14 ug/1 d

HIGHLIGHTS OF PRESCRIBING INFORMATION

These highlights do not include all the information needed to use MENOSTAR safely and effectively. See full prescribing information for MENOSTAR.
Menostar® (estradiol transdermal system)
Initial U.S. Approval: 1975

RECENT MAJOR CHANGES

Warnings and Precautions (5.2) 12/2023

WARNING: ENDOMETRIAL CANCER, CARDIOVASCULAR DISORDERS, PROBABLE DEMENTIA and BREAST CANCER

See full prescribing information for complete boxed warning.

Estrogen-Alone Therapy

- There is an increased risk of endometrial cancer in a woman with a uterus who uses unopposed estrogens (5.2)
- The Women’s Health Initiative (WHI) estrogen-alone substudy reported increased risks of stroke and deep vein thrombosis (DVT) (5.1)
- The WHI Memory Study (WHIMS) estrogen-alone ancillary study of WHI reported an increased risk of probable dementia in postmenopausal women 65 years of age and older (5.3)
- Do not use estrogen-alone therapy for the prevention of cardiovascular disease or dementia (5.1, 5.3)

Estrogen Plus Progestin Therapy

- The WHI estrogen plus progestin substudy reported increased risks of stroke, DVT, pulmonary embolism (PE), and myocardial infarction (MI) (5.1)
- The WHI estrogen plus progestin substudy reported increased risks of invasive breast cancer (5.2)
- The WHIMS estrogen plus progestin ancillary study of WHI reported an increased risk of probable dementia in postmenopausal women 65 years of age and older (5.3)
- Do not use estrogen plus progestogen therapy for the prevention of cardiovascular disease or dementia (5.1, 5.3)

1 INDICATIONS AND USAGE

Menostar is an estrogen indicated for:

- Prevention of Postmenopausal Osteoporosis (1.1)
  Limitations of Use
  When prescribing solely for the prevention of postmenopausal osteoporosis, first consider the use of non-estrogen medications. Consider estrogen therapy only for women at significant risk of osteoporosis.

2 DOSAGE AND ADMINISTRATION

- Apply Menostar once-weekly to the lower abdomen. Do not apply Menostar to the breast. (2.1)

3 DOSAGE FORMS AND STRENGTHS

- Transdermal system: 14 mcg per day (3)

4 CONTRAINDICATIONS

- Undiagnosed abnormal genital bleeding (4, 5.2)
- Breast cancer or a history of breast cancer (4, 5.2)
- Estrogen-dependent neoplasia (4, 5.2)
- Active DVT, PE or a history of these conditions (4, 5.1)
- Active arterial thromboembolic disease (for example, stroke or MI), or a history of these conditions (4, 5.1)
- Known anaphylactic reaction, or angioedema, or hypersensitivity to Menostar (4)
- Hepatic impairment or disease (4, 5.10)
- Protein C, protein S, or antithrombin deficiency, or other known thrombophilic disorders (4)

5 WARNINGS AND PRECAUTIONS

- Estrogens increase the risk of gallbladder disease (5.4)
- Discontinue estrogens if severe hypercalcemia, loss of vision, severe hypertriglyceridemia or cholestatic jaundice occurs (5.5, 5.6, 5.9, 5.10)
- Monitor thyroid function in women on thyroid hormone replacement therapy (5.11, 5.18)

6 ADVERSE REACTIONS

The most common adverse reactions (≥ 10 percent) with Menostar are: upper respiratory tract infections, pain, arthralgia, and leukorrhea. (6.1)

To report SUSPECTED ADVERSE REACTIONS, contact Bayer HealthCare Pharmaceuticals Inc. at 1-888-84-BAYER (1-888-842-2937) or FDA at 1-800-FDA-1088 or www.fda.gov/medwatch.

7 DRUG INTERACTIONS

- Inducers and/or inhibitors of CYP3A4 may affect estrogen drug metabolism and decrease or increase the estrogen plasma concentration. (7)

FULL PRESCRIBING INFORMATION

WARNING: ENDOMETRIAL CANCER, CARDIOVASCULAR DISORDERS, PROBABLE DEMENTIA and BREAST CANCER

Estrogen-Alone Therapy

Endometrial Cancer

There is an increased risk of endometrial cancer in a woman with a uterus who uses unopposed estrogens. Adding a progestogen to estrogen therapy has been shown to reduce the risk of endometrial hyperplasia, which may be a precursor to endometrial cancer. Perform adequate diagnostic measures, including directed or random endometrial sampling when indicated to rule out malignancy in postmenopausal women with undiagnosed, persistent or recurring abnormal genital bleeding [see Warnings and Precautions (5.2)].

Cardiovascular Disorders and Probable Dementia

The Women’s Health Initiative (WHI) estrogen-alone substudy reported increased risks of stroke and deep vein thrombosis (DVT) in postmenopausal women (50 to 79 years of age) during 7.1 years of treatment with daily oral conjugated estrogens (CE) [0.625 mg]-alone, relative to placebo [see Warnings and Precautions (5.1), and Clinical Studies (14.2)].

The WHI Memory Study (WHIMS) estrogen-alone ancillary study of WHI reported an increased risk of developing probable dementia in postmenopausal women 65 years of age and older during 5.2 years of treatment with daily CE (0.625 mg)-alone, relative to placebo. It is unknown whether this finding applies to younger postmenopausal women [see Warnings and Precautions (5.3), Use in Specific Populations (8.5), and Clinical Studies (14.3)].

Do not use estrogen-alone therapy for the prevention of cardiovascular disease or dementia [see Warnings and Precautions (5.1, 5.3), and Clinical Studies (14.2, 14.3)].

Only daily oral 0.625 mg CE was studied in the estrogen-alone substudy of the WHI. Therefore, the relevance of the WHI findings regarding adverse cardiovascular events and dementia to lower CE doses, other routes of administration, or other estrogen-alone products is not known. Without such data, it is not possible to definitively exclude these risks or determine the extent of these risks for other products. Discuss with your patient the benefits and risks of estrogen-alone therapy, taking into account her individual risk profile. Prescribe estrogens with or without progestogens at the lowest effective doses and for the shortest duration consistent with treatment goals and risks for the individual woman.

Estrogen Plus Progestin Therapy

Cardiovascular Disorders and Probable Dementia

The WHI estrogen plus progestin substudy reported increased risks of DVT, pulmonary embolism (PE), stroke and myocardial infarction (MI) in postmenopausal women (50 to 79 years of age) during 5.6 years of treatment with daily oral CE (0.625 mg) combined with medroxyprogesterone acetate (MPA) [2.5 mg], relative to placebo [see Warnings and Precautions (5.1), and Clinical Studies (14.2)].

The WHIMS estrogen plus progestin ancillary study of the WHI reported an increased risk of developing probable dementia in postmenopausal women 65 years of age and older during 4 years of treatment with daily CE (0.625 mg) combined with MPA (2.5 mg), relative to placebo. It is unknown whether this finding applies to younger postmenopausal women [see Warnings and Precautions (5.3), Use in Specific Populations (8.5), and Clinical Studies (14.3)].

Do not use estrogen plus progestogen therapy for the prevention of cardiovascular disease or dementia [see Warnings and Precautions (5.1, 5.3), and Clinical Studies (14.2, 14.3)].

Breast Cancer

The WHI estrogen plus progestin substudy also demonstrated an increased risk of invasive breast cancer [see Warnings and Precautions (5.2), and Clinical Studies (14.2)].

Only daily oral 0.625 mg CE and 2.5 mg MPA were studied in the estrogen plus progestin substudy of the WHI. Therefore, the relevance of the WHI findings regarding adverse cardiovascular events, dementia and breast cancer to lower CE plus other MPA doses, other routes of administration, or other estrogen plus progestogen products is not known. Without such data, it is not possible to definitively exclude these risks or determine the extent of these risks for other products. Discuss with your patient the benefits and risks of estrogen plus progestogen therapy, taking into account her individual risk profile.

Prescribe estrogens with or without progestogens at the lowest effective doses and for the shortest duration consistent with treatment goals and risks for the individual woman.

1 INDICATIONS AND USAGE

Menostar is indicated for:

1.1 Prevention of Postmenopausal Osteoporosis

Limitation of Use

When prescribing solely for the prevention of postmenopausal osteoporosis, first consider the use of non-estrogen medications. Consider estrogen therapy only for women at significant risk of osteoporosis.

2 DOSAGE AND ADMINISTRATION

Generally, when estrogen is prescribed for a postmenopausal woman with a uterus, consider addition of a progestogen to reduce the risk of endometrial cancer. Generally a woman without a uterus does not need to take a progestogen in addition to her estrogen therapy. In some cases, however, hysterectomized women who have a history of endometriosis may need a progestogen [see Warnings and Precautions (5.2, 5.14)].

Use estrogen-alone, or in combination with a progestogen at the lowest effective dose and for the shortest duration consistent with treatment goals and risks for the individual woman. Reevaluate postmenopausal women periodically as clinically appropriate to determine if treatment is still necessary.

2.1 Prevention of Postmenopausal Osteoporosis

Apply Menostar 14 mcg per day to a clean dry area of the lower abdomen once weekly.

2.2 Application of the Menostar Transdermal System

Site Selection

- Place the adhesive side of Menostar on a clean, dry area of the lower abdomen or the upper quadrant of the buttock.
- Do not apply Menostar to or near the breasts.
- Rotate the sites of application with an interval of at least 1-week allowed between applications to a same site.
- Select an area that is not oily, damaged, or irritated. Avoid the waistline, since tight clothing may rub the transdermal system off.
- Avoid application to areas where sitting would dislodge Menostar.

Application

- Apply Menostar immediately after opening the pouch and removing the protective liner.
- Press Menostar firmly in place with the fingers for at least 10 seconds, making sure there is good contact, especially around the edges.
- If the system lifts, apply pressure to maintain adhesion.
- In the event that a system falls off, reapply it to a different location. If the old system cannot be reapplied, apply a new system for the remainder of the 7-day dosing interval.
- Wear only one system at any one time during the 7-day dosing interval.
- Swimming, bathing, or using a sauna while using Menostar has not been studied, and these activities may decrease the adhesion of the system and the delivery of estradiol.

2.3 Removal of the Menostar Transdermal System

- Remove Menostar carefully and slowly to avoid irritation of the skin.
- If any adhesive remains on the skin after removal of Menostar, allow the area to dry for 15 minutes and then gently rub the area with an oil-based cream or lotion to remove the adhesive residue.
- Used patches still contain some active hormones. Carefully fold each patch in half so that it sticks to itself before throwing it away.

3 DOSAGE FORMS AND STRENGTHS

Menostar (estradiol transdermal system) 14 mcg per day - each 3.25 cm^2 system contains 1 mg of estradiol.

4 CONTRAINDICATIONS

Menostar is contraindicated in women with any of the following conditions:

- Undiagnosed abnormal genital bleeding [see Warnings and Precautions (5.2)]
- Breast cancer or history of breast cancer [see Warnings and Precautions (5.2)]
- Estrogen-dependent neoplasia [see Warnings and Precautions (5.2)]
- Active DVT, PE, or a history of these conditions [see Warnings and Precautions (5.1)]
- Active arterial thromboembolic disease (for example, stroke or MI), or a history of these conditions [see Warnings and Precautions (5.1)]
- Known anaphylactic reaction, or angioedema, or hypersensitivity to Menostar
- Hepatic impairment or disease
- Protein C, protein S, or antithrombin deficiency, or other known thrombophilic disorders

5 WARNINGS AND PRECAUTIONS

5.1 Cardiovascular Disorders

Increased risks of stroke and DVT are reported with estrogen-alone therapy. Increased risks of PE, DVT, stroke and MI are reported with estrogen plus progestin therapy. Immediately discontinue estrogen with or without progestogen therapy if any of these occur or are suspected.

Manage appropriately any risk factors for arterial vascular disease (for example, hypertension, diabetes mellitus, tobacco use, hypercholesterolemia, and obesity) and/or venous thromboembolism (VTE) (for example, personal history or family history of VTE, obesity, and systemic lupus erythematosus).

Stroke

The WHI estrogen-alone substudy reported a statistically significant increased risk of stroke in women 50 to 79 years of age receiving daily CE (0.625 mg)-alone compared to women in the same age group receiving placebo (45 versus 33 strokes per 10,000 women-years, respectively). The increase in risk was demonstrated in year 1 and persisted [see Clinical Studies (14.2)]. Immediately discontinue estrogen-alone therapy if a stroke occurs or is suspected.

Subgroup analyses of women 50 to 59 years of age suggest no increased risk of stroke for those women receiving CE (0.625 mg)-alone versus those receiving placebo (18 versus 21 per 10,000 women-years).^1

The WHI estrogen plus progestin substudy reported a statistically significant increased risk of stroke in women 50 to 79 years of age receiving daily CE (0.625 mg) plus MPA (2.5 mg) compared to women in the same age group receiving placebo (33 versus 25 strokes per 10,000 women years, respectively) [see Clinical Studies (14.2)]. The increase in risk was demonstrated after the first year and persisted.^1 Immediately discontinue estrogen plus progestogen therapy if a stroke occurs or is suspected.

Coronary Heart Disease

The WHI estrogen-alone substudy reported no overall effect on coronary heart disease (CHD) events (defined as nonfatal MI, silent MI, or CHD death) in women receiving estrogen-alone compared to placebo^2 [see Clinical Studies (14.2)].

Subgroup analyses of women 50 to 59 years of age, who were less than 10 years since menopause, suggest a reduction (not statistically significant) of CHD events in those women receiving daily CE (0.625 mg)-alone compared to placebo (8 versus 16 per 10,000 women-years).^1

The WHI estrogen plus progestin substudy reported an increased risk (not statistically significant) of CHD events in women receiving daily CE (0.625 mg) plus MPA (2.5 mg) compared to women receiving placebo (41 versus 34 per 10,000 women-years).^1 An increase in relative risk was demonstrated in year 1, and a trend toward decreasing relative risk was reported in years 2 through 5 [see Clinical Studies (14.2)].

In postmenopausal women with documented heart disease (n = 2,763), average 66.7 years of age, in a controlled clinical trial of secondary prevention of cardiovascular disease (Heart and Estrogen/Progestin Replacement Study; HERS), treatment with daily CE (0.625 mg) plus MPA (2.5 mg) demonstrated no cardiovascular benefit. During an average follow-up of 4.1 years, treatment with CE plus MPA did not reduce the overall rate of CHD events in postmenopausal women with established CHD. There were more CHD events in the CE plus MPA-treated group than in the placebo group in year 1, but not during the subsequent years. Two thousand three hundred twenty-one (2,321) women from the original HERS trial agreed to participate in an open label extension of HERS, HERS II. Average follow-up in HERS II was an additional 2.7 years, for a total of 6.8 years overall. Rates of CHD events were comparable among women in the CE plus MPA group and the placebo group in HERS, HERS II, and overall.

Venous Thromboembolism

In the WHI estrogen-alone substudy, the risk of VTE (DVT and PE) was increased for women receiving daily CE (0.625 mg)-alone compared to placebo (30 versus 22 per 10,000 women-years), although only the increased risk of DVT reached statistical significance (23 versus 15 per 10,000 women-years). The increase in VTE risk was demonstrated during the first 2 years^3 [see Clinical Studies (14.2)]. Immediately discontinue estrogen-alone therapy if VTE occurs or is suspected.

The WHI estrogen plus progestin substudy reported a statistically significant 2-fold greater rate of VTE in women receiving daily CE (0.625 mg) plus MPA (2.5 mg) compared to women receiving placebo (35 versus 17 per 10,000 women-years). Statistically significant increases in risk for both DVT (26 versus 13 per 10,000 women-years) and PE (18 versus 8 per 10,000 women-years) were also demonstrated. The increase in VTE risk was demonstrated during the first year and persisted^4 [see Clinical Studies (14.2)]. Immediately discontinue estrogen plus progestogen therapy if a VTE occurs or is suspected.

If feasible, discontinue estrogens at least 4 to 6 weeks before surgery of the type associated with an increased risk of thromboembolism, or during periods of prolonged immobilization.

5.2 Malignant Neoplasms

Endometrial Cancer

An increased risk of endometrial cancer has been reported with the use of unopposed estrogen therapy in a woman with a uterus. The reported endometrial cancer risk among unopposed estrogen users is about 2 to 12 times greater than in non-users and appears dependent on duration of treatment and on estrogen dose. Most studies show no significant increased risk associated with use of estrogens for less than 1 year. The greatest risk appears associated with prolonged use, with increased risks of 15- to 24-fold for 5 to 10 years or more, and this risk has been shown to persist for at least 8 to 15 years after estrogen therapy is discontinued.

Clinical surveillance of all women using estrogen-alone or estrogen plus progestogen therapy is important. Perform adequate diagnostic measures, including directed or random endometrial sampling when indicated to rule out malignancy in postmenopausal women with undiagnosed persistent or recurring abnormal genital bleeding with unknown etiology.

There is no evidence that the use of natural estrogens results in a different endometrial risk profile than synthetic estrogens of equivalent estrogen dose. Adding a progestogen to estrogen therapy in postmenopausal women has been shown to reduce the risk of endometrial hyperplasia, which may be a precursor to endometrial cancer.

Breast Cancer

The WHI substudy of daily CE (0.625 mg)-alone provided information about breast cancer in estrogen-alone users. In the WHI estrogen-alone substudy, after an average follow-up of 7.1 years, daily CE (0.625mg)-alone was not associated with an increased risk of invasive breast cancer [relative risk (RR) 0.80]^5 [see Clinical Studies (14.2)].

After a mean follow-up of 5.6 years, the WHI substudy of daily CE (0.625 mg) plus MPA (2.5 mg) reported an increased risk of invasive breast cancer in women who took daily CE plus MPA compared to placebo.

In this substudy, prior use of estrogen-alone or estrogen plus progestin therapy was reported by 26 percent of the women. The relative risk of invasive breast cancer was 1.24, and the absolute risk was 41 versus 33 cases per 10,000 women-years, for CE plus MPA compared with placebo [see Clinical Studies (14.2)]. Among women who reported prior use of hormone therapy, the relative risk of invasive breast cancer was 1.86, and the absolute risk was 46 versus 25 cases per 10,000 women-years for CE plus MPA compared with placebo.^6 Among women who reported no prior use of hormone therapy, the relative risk of invasive breast cancer was 1.09, and the absolute risk was 40 versus 36 cases per 10,000 women-years for CE plus MPA compared with placebo. In the same substudy, invasive breast cancers were larger, were more likely to be node positive, and were diagnosed at a more advanced stage in the CE (0.625 mg) plus MPA (2.5 mg) group compared with the placebo group. Metastatic disease was rare, with no apparent difference between the two groups. Other prognostic factors, such as histologic subtype, grade and hormone receptor status did not differ between the groups^6 [see Clinical Studies (14.2)].

Consistent with the WHI clinical trial, observational studies have also reported an increased risk of breast cancer with estrogen plus progestin therapy, and a smaller increase in the risk for breast cancer with estrogen-alone therapy, after several years of use. One large meta-analysis of prospective cohort studies reported increased risks that were dependent upon duration of use and could last up to >10 years after discontinuation of estrogen plus progestin therapy and estrogen-alone therapy. Extension of the WHI trials also demonstrated increased breast cancer risk associated with estrogen plus progestin therapy. Observational studies also suggest that the risk of breast cancer was greater, and became apparent earlier, with estrogen plus progestin therapy as compared to estrogen-alone therapy. These studies have not generally found significant variation in the risk of breast cancer among different estrogen plus progestin combinations, doses, or routes of administration.

The use of estrogen-alone and estrogen plus progestin has been reported to result in an increase in abnormal mammograms requiring further evaluation.

All women should receive yearly breast examinations by a healthcare provider and perform monthly breast self-examinations. In addition, mammography examinations should be scheduled based on patient age, risk factors, and prior mammogram results.

Ovarian Cancer

The CE plus MPA substudy of WHI reported that estrogen plus progestin increased the risk of ovarian cancer. After an average follow-up of 5.6 years, the relative risk for CE plus MPA versus placebo was 1.58 (95 percent CI, 0.77-3.24), but it was not statistically significant. The absolute risk for CE plus MPA versus placebo was 4 versus 3 cases per 10,000 women-years.^7

A meta-analysis of 17 prospective and 35 retrospective epidemiology studies found that women who used hormonal therapy for menopausal symptoms had an increased risk for ovarian cancer. The primary analysis, using case-control comparisons, included 12,110 cancer cases from the 17 prospective studies. The relative risks associated with current use of hormonal therapy was 1.41 (95% confidence interval [CI] 1.32 to 1.50); there was no difference in the risk estimates by duration of the exposure (less than 5 years [median of 3 years]vs. greater than 5 years [median of 10 years] of use before the cancer diagnosis). The relative risk associated with combined current and recent use (discontinued use within 5 years before cancer diagnosis) was 1.37 (95% CI 1.27 to 1.48), and the elevated risk was significant for both estrogen-alone and estrogen plus progestin products. The exact duration of hormone therapy use associated with an increased risk of ovarian cancer, however, is unknown.

5.3 Probable Dementia

In the WHI Memory Study (WHIMS) estrogen-alone ancillary study, a population of 2,947 hysterectomized women 65 to 79 years of age were randomized to daily CE (0.625 mg)-alone or placebo.

After an average follow-up of 5.2 years, 28 women in the estrogen-alone group and 19 women in the placebo group were diagnosed with probable dementia. The relative risk of probable dementia for CE-alone versus placebo was 1.49 (95 percent CI, 0.83-2.66). The absolute risk of probable dementia for CE-alone versus placebo was 37 versus 25 cases per 10,000 women-years^8 [see Use in Specific Populations (8.5), and Clinical Studies (14.3)].

In the WHIMS estrogen plus progestin ancillary study, a population of 4,532 postmenopausal women 65 to 79 years of age was randomized to daily CE (0.625 mg) plus MPA (2.5 mg) or placebo. After an average follow-up of 4 years, 40 women in the CE plus MPA group and 21 women in the placebo group were diagnosed with probable dementia.The relative risk of probable dementia for CE plus MPA versus placebo was 2.05 (95 percent CI, 1.21-3.48). The absolute risk of probable dementia for CE plus MPA versus placebo was 45 versus 22 cases per 10,000 women-years^8 [see Use in Specific Populations (8.5), and Clinical Studies (14.3)].

When data from the two populations in the WHIMS estrogen-alone and estrogen plus progestin ancillary studies were pooled as planned in the WHIMS protocol, the reported overall relative risk for probable dementia was 1.76 (95 percent CI, 1.19-2.60). Since both ancillary studies were conducted in women 65 to 79 years of age, it is unknown whether these findings apply to younger postmenopausal women^8 [see Use in Specific Populations (8.5), and Clinical Studies (14.3)].

5.4 Gallbladder Disease

A 2- to 4-fold increase in the risk of gallbladder disease requiring surgery in postmenopausal women receiving estrogens has been reported.

5.5 Hypercalcemia

Estrogen administration may lead to severe hypercalcemia in women with breast cancer and bone metastases. Discontinue estrogens, including Menostar if hypercalcemia occurs, and take appropriate measures to reduce the serum calcium level.

5.6 Visual Abnormalities

Retinal vascular thrombosis has been reported in women receiving estrogens. Discontinue Menostar pending examination if there is sudden partial or complete loss of vision, or a sudden onset of proptosis, diplopia, or migraine. Permanently discontinue estrogens, including Menostar, if examination reveals papilledema or retinal vascular lesions.

5.7 Addition of a Progestogen When a Woman Has Not Had a Hysterectomy

Studies of the addition of a progestogen for 10 or more days of a cycle of estrogen administration, or daily with estrogen in a continuous regimen, have reported a lowered incidence of endometrial hyperplasia than would be induced by estrogen treatment alone. Endometrial hyperplasia may be a precursor to endometrial cancer.

There are, however, possible risks that may be associated with the use of progestogens with estrogens compared to estrogen-alone regimens. These include an increased risk of breast cancer.

5.8 Elevated Blood Pressure

In a small number of case reports, substantial increases in blood pressure have been attributed to idiosyncratic reactions to estrogens. In a large, randomized, placebo-controlled clinical trial, a generalized effect of estrogens on blood pressure was not seen.

5.9 Exacerbation of Hypertriglyceridemia

In women with pre-existing hypertriglyceridemia, estrogen therapy may be associated with elevations of plasma triglycerides leading to pancreatitis. Discontinue Menostar if pancreatitis occurs.

5.10 Hepatic Impairment and/or Past History of Cholestatic Jaundice

Estrogens may be poorly metabolized in women with hepatic impairment. Exercise caution in any woman with a history of cholestatic jaundice associated with past estrogen use or with pregnancy. In the case of recurrence of cholestatic jaundice, discontinue Menostar.

5.11 Exacerbation of Hypothyroidism

Estrogen administration leads to increased thyroid-binding globulin (TBG) levels. Women with normal thyroid function can compensate for the increased TBG by making more thyroid hormone, thus maintaining free T4 and T3 serum concentrations in the normal range. Women dependent on thyroid hormone replacement therapy who are also receiving estrogens may require increased doses of their thyroid replacement therapy. Monitor thyroid function in these women during treatment with Menostar to maintain their free thyroid hormone levels in an acceptable range.

5.12 Fluid Retention

Estrogens may cause some degree of fluid retention. Monitor any woman with a condition(s) that might predispose her to fluid retention, such as a cardiac or renal impairment. Discontinue estrogen-alone therapy, including Menostar, with evidence of medically concerning fluid retention.

5.13 Hypocalcemia

Estrogen-induced hypocalcemia may occur in women with hypoparathyroidism. Consider whether the benefits of estrogen therapy, including Menostar, outweigh the risks in such women.

5.14 Exacerbation of Endometriosis

A few cases of malignant transformation of residual endometrial implants have been reported in women treated post-hysterectomy with estrogen-alone therapy. Consider the addition of progestogen therapy for women known to have residual endometriosis post-hysterectomy.

5.15 Hereditary Angioedema

Exogenous estrogens may exacerbate symptoms of angioedema in women with hereditary angioedema. Consider whether the benefits of estrogen therapy, including Menostar, outweigh the risks in such women.

5.16 Exacerbation of Other Conditions

Estrogen therapy, including Menostar, may cause an exacerbation of asthma, diabetes mellitus, epilepsy, migraine, porphyria, systemic lupus erythematosus, and hepatic hemangiomas. Consider whether the benefits of estrogen therapy outweigh the risks in such women.

5.17 Laboratory Tests

Serum follicle stimulating hormone (FSH) and estradiol levels have not been shown to be useful in the management of postmenopausal women using Menostar for the prevention of postmenopausal osteoporosis.

5.18 Drug-Laboratory Test Interactions

- Accelerated prothrombin time, partial thromboplastin time, and platelet aggregation time; increased platelet count; increased factors II, VII antigen, VIII antigen, VIII coagulant activity, IX, X, XII, VII-X complex, II-VII-X complex, and beta-thromboglobulin; decreased levels of antifactor Xa and antithrombin III, decreased antithrombin III activity; increased levels of fibrinogen and fibrinogen activity; increased plasminogen antigen and activity.
- Increased TBG levels leading to increased circulating total thyroid hormone, as measured by protein-bound iodine (PBI), T4 levels (by column or by radioimmunoassay) or T3 levels by radioimmunoassay. T3 resin uptake is decreased, reflecting the elevated TBG. Free T4 and free T3 concentrations are unaltered. Women on thyroid replacement therapy may require higher doses of thyroid hormone.
- Other binding proteins may be elevated in serum, for example, corticosteroid binding globulin (CBG), sex hormone-binding globulin (SHBG), leading to increased total circulating corticosteroids and sex steroids, respectively. Free hormone concentrations, such as testosterone and estradiol, may be decreased. Other plasma proteins may be increased (angiotensinogen/renin substrate, alpha-l-antitrypsin, ceruloplasmin).
- Increased plasma high-density lipoprotein (HDL) and HDL2 cholesterol subfraction concentrations, reduced low-density lipoprotein (LDL) cholesterol concentration, and increased triglyceride levels.
- Impaired glucose tolerance.

6 ADVERSE REACTIONS

The following serious adverse reactions are discussed elsewhere in the labeling:

- Cardiovascular Disorders [see Boxed Warning, Warnings and Precautions (5.1)]
- Malignant Neoplasms [see Boxed Warning, Warnings and Precautions (5.2)]

6.1 Clinical Trials Experience

Because clinical trials are conducted under widely varying conditions, adverse reaction rates observed in the clinical trials of a drug cannot be directly compared to rates in the clinical trials of another drug and may not reflect the rates observed in practice.

Menostar was investigated in a 2-year double blind, placebo-controlled, multicenter study in the United States. A total of 417 postmenopausal women (208 women on Menostar, 209 on placebo) 60 to 80 years old, with an intact uterus were enrolled in the study. At 24 months, 189 women remained in the Menostar group and 186 remained in the placebo group. Adverse events with an incidence of ≥5 percent in the Menostar 14 mcg group and greater than those reported in the placebo group are listed in Table 1.

Table 1: Summary of Most Frequently Reported Treatment Emergent Adverse Reactions (≥5 percent) by Treatment Groups
Body System; Adverse Reactions | Menostar 14 mcg/day; (N=208) | Placebo; (N=209)
Body as a Whole | 95 (46%) | 100 (48%)
Abdominal Pain | 17 (8%) | 17 (8%)
Accidental Injury | 29 (14%) | 23 (11%)
Infection | 11 (5%) | 10 (5%)
Pain | 26 (13%) | 26 (12%)
Cardiovascular | 20 (10%) | 19 (9%)
Digestive System | 52 (25%) | 44 (21%)
Constipation | 11 (5%) | 6 (3%)
Dyspepsia | 11 (5%) | 9 (4%)
Metabolic and Nutritional Disorders | 25 (12%) | 22 (11%)
Musculoskeletal System | 54 (26%) | 51 (24%)
Arthralgia | 24 (12%) | 13 (6%)
Arthritis | 11 (5%) | 15 (7%)
Myalgia | 10 (5%) | 6 (3%)
Nervous System | 30 (14%) | 23 (11%)
Dizziness | 11 (5%) | 6 (3%)
Respiratory System | 62 (30%) | 67 (32%)
Bronchitis | 12 (6%) | 9 (4%)
Upper Respiratory Infection | 33 (16%) | 35 (17%)
Skin and Appendages | 50 (24%) | 54 (26%)
Application Site Reaction | 18 (9%) | 18 (9%)
Breast Pain | 10 (5%) | 8 (4%)
Urogenital System | 66 (32%) | 40 (19%)
Cervical Polyps | 13 (6%) | 4 (2%)
Leukorrhea | 22 (11%) | 3 (1%)

6.2 Postmarketing Experience

The following adverse reactions have been identified during post-approval use of Climara and Menostar. Because these reactions are reported voluntarily from a population of uncertain size, it is not always possible to reliably estimate their frequency or establish a causal relationship to drug exposure.

Genitourinary System

Changes in bleeding pattern, pelvic pain

Breast

Breast cancer, breast pain, breast tenderness

Cardiovascular

Changes in blood pressure, palpitations, hot flashes

Gastrointestinal

Vomiting, abdominal pain, abdominal distension, nausea

Skin

Alopecia, hyperhidrosis, night sweats, urticaria, rash

Eyes

Visual disturbances, contact lens intolerance

Central Nervous System

Depression, migraine, paresthesia, dizziness, anxiety, irritability, mood swings, nervousness, insomnia, headache

Miscellaneous

Edema, fatigue, menopausal symptoms, weight increased, application site reaction, anaphylactic reactions

7 DRUG INTERACTIONS

In vitro and in vivo studies have shown that estrogens are metabolized partially by cytochrome P450 3A4 (CYP3A4). Therefore, inducers or inhibitors of CYP3A4 may affect estrogen drug metabolism. Inducers of CYP3A4 such as St. John’s wort (hypericum perforatum) preparations, phenobarbital, carbamazepine, and rifampin may reduce plasma concentrations of estrogens, possibly resulting in a decrease in therapeutic effects and/or changes in the uterine bleeding profile. Inhibitors of CYP3A4 such as erythromycin, clarithromycin, ketoconazole, itraconazole, ritonavir and grapefruit juice may increase plasma concentrations of estrogens and may result in adverse reactions.

8 USE IN SPECIFIC POPULATIONS

8.1 Pregnancy

Risk Summary

Menostar is not indicated for use in pregnancy. There are no data with the use of Menostar in pregnant women, however, epidemiologic studies and meta-analyses have not found an increased risk of genital or non-genital birth defects (including cardiac anomalies and limb reduction defects) following exposure to combined hormonal contraceptives (estrogens and progestins) before conception or during early pregnancy.

In the U.S. general population, the estimated background risk of major birth defects and miscarriage in clinically recognized pregnancies is 2 to 4% and 15 to 20%, respectively.

8.2 Lactation

Risk Summary

Estrogens are present in human milk and can reduce milk production in breast-feeding females. This reduction can occur at any time but is less likely to occur once breast-feeding is well-established. The developmental and health benefits of breastfeeding should be considered along with the mother’s clinical need for Menostar and any potential adverse effects on the breastfed child from Menostar or from the underlying maternal condition.

8.4 Pediatric Use

Menostar is not indicated for use in pediatric patients. Clinical studies have not been conducted in the pediatric population.

8.5 Geriatric Use

A total of 417 postmenopausal women 61 to 79 years old, with an intact uterus, participated in the osteoporosis trial. More than 50 percent of women receiving study drug, were 65 years of age or older. Efficacy in older (≥ 65 years of age) and younger (<65 years of age) postmenopausal women in the osteoporosis treatment trial was comparable both at 12 and 24 months. Safety in older (≥ 65 years of age) and younger (<65 years of age) postmenopausal women in the osteoporosis treatment trial was also comparable throughout the study.

The Women’s Health Initiative Studies

In the WHI estrogen-alone substudy (daily CE [0.625 mg]-alone versus placebo), there was a higher relative risk of stroke in women greater than 65 years of age [see Clinical Studies (14.2)].

In the WHI estrogen plus progestin substudy (daily CE [0.625 mg] plus MPA [2.5 mg] versus placebo), there was a higher relative risk of nonfatal stroke and invasive breast cancer in women greater than 65 years of age [see Clinical Studies (14.2)].

The Women’s Health Initiative Memory Study

In the WHIMS ancillary studies of postmenopausal women 65 to 79 years of age, there was an increased risk of developing probable dementia in women receiving estrogen-alone or estrogen plus progestin when compared to placebo [see Warnings and Precautions (5.3), and Clinical Studies (14.3)].

Since both ancillary studies were conducted in women 65 to 79 years of age, it is unknown whether these findings apply to younger postmenopausal women^8 [see Warnings and Precautions (5.3), and Clinical Studies (14.3)].

10 OVERDOSAGE

Overdosage of estrogen may cause nausea and vomiting, breast tenderness, abdominal pain, drowsiness and fatigue, and withdrawal bleeding in women. Treatment of overdose consists of discontinuation of Menostar therapy with institution of appropriate symptomatic care.

11 DESCRIPTION

Menostar (estradiol transdermal system) is designed to provide nominal in vivo delivery of 14 mcg of estradiol per day continuously upon application to intact skin. The period of use is 7 days. The transdermal system has a contact surface area of 3.25 cm^2, and contains 1 mg of estradiol USP.

Estradiol USP is a white, crystalline powder, chemically described as estra-1,3,5(10)-triene-3, 17ß-diol. It has an empirical formula of C18H24O2 and molecular weight of 272.38. The structural formula is:

The Menostar transdermal system comprises three layers. Proceeding from the visible surface toward the surface attached to the skin, these layers are:

1. A translucent polyethylene film.

2. An acrylate adhesive matrix containing estradiol USP.

3. A protective liner of siliconized or fluoropolymer-coated polyester film is attached to the adhesive surface and must be removed before the transdermal system can be used.

The active component of the transdermal system is estradiol. The remaining components of the transdermal system (acrylate copolymer adhesive, fatty acid esters, and polyethylene backing) are pharmacologically inactive.

12 CLINICAL PHARMACOLOGY

12.1 Mechanism of Action

Endogenous estrogens are largely responsible for the development and maintenance of the female reproductive system and secondary sexual characteristics. Although circulating estrogens exist in a dynamic equilibrium of metabolic interconversions, estradiol is the principal intracellular human estrogen and is substantially more potent than its metabolites, estrone and estriol, at the receptor level.

The primary source of estrogen in normally cycling adult women is the ovarian follicle, which secretes 70 to 500 mcg of estradiol daily, depending on the phase of the menstrual cycle. After menopause, most endogenous estrogen is produced by conversion of androstenedione, which is secreted by the adrenal cortex, to estrone in the peripheral tissues. Thus, estrone and the sulfate conjugated form, estrone sulfate, are the most abundant circulating estrogens in postmenopausal women.

Estrogens act through binding to nuclear receptors in estrogen-responsive tissues. To date, two estrogen receptors have been identified. These vary in proportion from tissue to tissue.

Circulating estrogens modulate the pituitary secretion of the gonadotropins, luteinizing hormone (LH) and follicle stimulating hormone (FSH), through a negative feedback mechanism. Estrogens act to reduce the elevated levels of these hormones seen in postmenopausal women.

12.2 Pharmacodynamics

Generally, a serum estrogen concentration does not predict an individual woman’s therapeutic response to Menostar nor her risk for adverse outcomes. Likewise, exposure comparisons across different estrogen products to infer efficacy or safety for the individual woman may not be valid.

12.3 Pharmacokinetics

Absorption

The bioavailability of estradiol following application of a Menostar transdermal system, relative to that of a transdermal system delivering 25 mcg per day, was investigated in 18 healthy postmenopausal women, mean age 66 years (range 60 to 80 years). The mean serum estradiol concentrations upon administration of the two patches to the lower abdomen are shown in Figure 1. Transdermal administration of Menostar produced geometric mean serum concentration (Cavg) of estradiol of 13.7 pg/mL. No patches failed to adhere during the one week application period of both transdermal systems. Following application of the Menostar transdermal system to the abdomen, it is estimated to provide an average nominal in-vivo daily delivery of 14 mcg estradiol per day.

The Menostar transdermal delivery system continuously releases estradiol which is transported across intact skin leading to sustained circulating levels of estradiol during a 7-day treatment period. The systemic availability of estradiol after transdermal administration is about 20 times higher than that after oral administration. This difference is due to the absence of first pass metabolism when estradiol is given by the transdermal route.

Figure 1: Mean Uncorrected Serum 17ß-Estradiol Concentrations vs. Time Profile Following Application of the Menostar Transdermal System and the Climara® 6.5 cm2 Transdermal System

Table 2 provides a summary of estradiol pharmacokinetic parameters determined during evaluation of the Menostar transdermal system using baseline uncorrected serum concentrations.

Table 2: Summary of Estradiol Pharmacokinetic Parameters (Abdomen Application)
Product | Estradiol Daily Delivery Rate, mcg/day | AUC (0-tlast) pg•h/mL | Cmax pg/mL | Cavg pg/mL | Tmax h | Cmin pg/mL
Menostar | 14 | 2296 | 20.6 | 13.7 | 42 | 12.6
Climara 6.5 cm^2 | 25 | 4151 | 37.2 | 24.7 | 42 | 20.4

Pharmacokinetic parameters are expressed in geometric means except for the Tmax which represents the median estimate and the Cmin which is expressed as the arithmetic mean. The estimated estradiol daily delivery rate for Climara 6.5 cm^2 is quoted from the Climara labeling.

Distribution

The distribution of exogenous estrogens is similar to that of endogenous estrogens. Estrogens are widely distributed in the body and are generally found in higher concentrations in the sex hormone target organs. Estrogens circulate in the blood largely bound to SHBG and albumin. In the clinical study with 208 patients on Menostar, SHBG concentration (mean ± SD) remained essentially unchanged over the 2 year period (baseline 45.1 ± 20.1 nmol/L, 24-month visit 46.4 ± 20.9 nmol/L).

Metabolism

Exogenous estrogens are metabolized in the same manner as endogenous estrogens. Circulating estrogens exist in a dynamic equilibrium of metabolic interconversions. These transformations take place mainly in the liver. Estradiol is converted reversibly to estrone, and both can be converted to estriol, which is a major urinary metabolite. Estrogens also undergo enterohepatic recirculation via sulfate and glucuronide conjugation in the liver, biliary secretion of conjugates into the intestine, and hydrolysis in the intestine followed by reabsorption. In postmenopausal women, a significant proportion of the circulating estrogens exist as sulfate conjugates, especially estrone sulfate, which serves as a circulating reservoir for the formation of more active estrogens.

Excretion

Estradiol, estrone, and estriol are excreted in the urine along with glucuronide and sulfate conjugates.

Adhesion

In a Menostar transdermal system pharmacokinetic study with 18 postmenopausal women, no patches failed to adhere during the one-week application period.

13 NONCLINICAL TOXICOLOGY

13.1 Carcinogenesis, Mutagenesis, Impairment of Fertility

Long-term continuous administration of natural and synthetic estrogens in certain animal species increases the frequency of carcinomas of the breast, uterus, cervix, vagina, testis, and liver.

14 CLINICAL STUDIES

14.1 Effects on Bone Mineral Density in Postmenopausal Women

The efficacy of Menostar in the prevention of postmenopausal osteoporosis was investigated in a 2-year double blind, placebo-controlled, multicenter study in the United States. A total of 417 postmenopausal women, 60 to 80 years of age, with an intact uterus were enrolled in the study. All participants received supplemental calcium and vitamin D.

At the lumbar spine Menostar increased BMD by 2.3 percent after 1 year and 3 percent after 2 years compared with a 0.5 percent increase after 1 and 2 years of treatment with placebo. At the hip Menostar increased BMD by 0.9 percent after one year and 0.84 percent after two years compared with a mean decrease of 0.22 percent after 1 year and 0.71 percent after 2 years of placebo treatment. The changes in BMD from baseline were statistically significantly (p <0.001) greater during treatment with Menostar than during treatment with placebo for both the spine and hip after 1 and 2 years (Table 3).

Table 3: Mean Percent BMD Change from Baseline in Lumbar Spine and Total Hip (Full Analysis Set)

Lumbar spine |  |  |  | Total hip
Time points | Menostar Na = 208 | Placebo Na = 209 | p-value | Time points | Menostar Na = 208 | Placebo Na = 209 | p-value
 | nb = 189 | nb = 186 |  |  | nb = 189 | nb =184
12-month Endpoint | +2.29 | +0.51 | < 0.001 | 12-month Endpoint | +0.90 | -0.22 | < 0.001
 | nb = 189 | nb = 186 |  |  | nb = 189 | nb = 185
24-month Endpoint | +2.99 | +0.54 | < 0.001 | 24-month Endpoint | +0.84 | -0.71 | < 0.001

a) N = total number of patients.
b) n = number of patients with data available for each variable.

The BMD data of the study were analyzed according to baseline estradiol levels of the patients. Overall, estimated treatment effects on lumbar spine and total hip BMD after 2 years were approximately twice as large in the subgroup with baseline estradiol levels < 5 pg/mL than in the subgroup with baseline estradiol levels ≥ 5 pg/mL (Table 4).

Table 4: Mean Percent Change in Lumbar Spine and Total Hip BMD at 24 months by Subgroups of Baseline Estradiol Level (< 5 pg/mL, 5 pg/mL)

Lumbar spine |  |  |  | Total hip
Baseline estradiol levels | Menostar | Placebo | Treatment difference | Menostar | Placebo | Treatment difference
< 5 pg/mL | na = 101 | na = 97 |  | na = 101 | na = 96
 | +3.50 | +0.29 | 3.21 | +1.04 | -1.09 | 2.13
 |  |  | (p < 0.001) |  |  | (p < 0.001)
≥ 5 pg/mL | na = 88 | na = 89 |  | na = 88 | na = 89
 | +2.40 | +0.81 | 1.59 | +0.61 | -0.31 | 0.92
 |  |  | (p = 0.002) |  |  | (p = 0.045)

a) n = number of patients with data available for each variable.

14.2 Women's Health Initiative Studies

The WHI enrolled approximately 27,000 predominantly healthy postmenopausal women in two substudies to assess the risks and benefits of daily oral CE (0.625 mg)-alone or in combination with MPA (2.5 mg) compared to placebo in the prevention of certain chronic diseases. The primary endpoint was the incidence of CHD (defined as nonfatal MI, silent MI and CHD death), with invasive breast cancer as the primary adverse outcome. A "global index" included the earliest occurrence of CHD, invasive breast cancer, stroke, PE, endometrial cancer (only in the CE plus MPA substudy), colorectal cancer, hip fracture, or death due to other causes. These substudies did not evaluate the effects of CE-alone or CE plus MPA on menopausal symptoms.

WHI Estrogen-Alone Substudy

The WHI estrogen-alone substudy was stopped early because an increased risk of stroke was observed, and it was deemed that no further information would be obtained regarding the risk and benefits of estrogen-alone in predetermined primary endpoints.

Results of the estrogen-alone substudy, which included 10,739 women (average 63 years of age, range 50 to 79: 75.3 percent White, 15.1 percent Black, 6.1 percent Hispanic, 3.6 percent Other) after an average follow-up of 7.1 years, are presented in Table 5.

Table 5: Relative and Absolute Risk Seen in the Estrogen-Alone Substudy of WHIa

Eventb | Relative Risk CE vs. Placebo (95% nCIb) | CE; n = 5,310 | Placebo; n = 5,429
Eventb | Relative Risk CE vs. Placebo (95% nCIb) | Absolute Risk per 10,000; Women-years
CHD eventsc | 0.95 (0.78-1.16) | 54 | 57
Non-fatal MIc | 0.91 (0.73-1.14) | 40 | 43
CHD deathc | 1.01 (0.71-1.43) | 16 | 16
All strokesc | 1.33 (1.05-1.68) | 45 | 33
Ischemic strokec | 1.55 (1.19-2.01) | 38 | 25
Deep vein thrombosisc,d | 1.47 (1.06-2.06) | 23 | 15
Pulmonary embolismc | 1.37 (0.90-2.07) | 14 | 10
Invasive breast cancerc | 0.8 (0.62-1.04) | 28 | 34
Colorectal cancerc | 1.08 (0.75-1.55) | 17 | 16
Hip fracturec | 0.65 (0.45-0.94) | 12 | 19
Vertebral fracturesc,d | 0.64 (0.44-0.93) | 11 | 18
Lower arm/wrist fracturesc,d | 0.58 (0.47-0.72) | 35 | 59
Total fracturesc,d | 0.71 (0.64-0.80) | 144 | 197
Death due to causese,f | 1.08 (0.88-1.32) | 53 | 50
Overall mortalityc,d | 1.04 (0.88-1.22) | 79 | 75
Global Indexg | 1.02 (0.92-1.13) | 206 | 201

a) Adapted from numerous WHI publications. WHI publications can be viewed at www.nhlbi.nih.gov/whi.
b) Nominal confidence intervals unadjusted for multiple looks and multiple comparisons.
c) Results are based on centrally adjudicated data for an average follow-up of 7.1 years.
d) Not included in “global index”.
e) Results are based on an average follow-up of 6.8 years.
f) All deaths, except from breast or colorectal cancer, definite or probable CHD, PE or cerebrovascular disease.
g) A subset of the events was combined in a "global index", defined as the earliest occurrence of CHD events, invasive breast cancer, stroke, pulmonary embolism, endometrial cancer, colorectal cancer, hip fracture, or death due to other causes.

For those outcomes included in the WHI "global index" that reached statistical significance, the absolute excess risks per 10,000 women-years in the group treated with CE-alone was 12 more strokes, while the absolute risk reduction per 10,000 women-years was 7 fewer hip fractures.^9 The absolute excess risk of events included in the "global index" was a non-significant 5 events per 10,000 women-years. There was no difference between the groups in terms of all-cause mortality.

No overall difference for primary CHD events (nonfatal MI, silent MI and CHD death) and invasive breast cancer incidence in women receiving CE-alone compared with placebo was reported in final centrally adjudicated results from the estrogen-alone substudy, after an average follow-up of 7.1 years. See Table 5.

Centrally adjudicated results for stroke events from the estrogen-alone substudy, after an average follow-up of 7.1 years, reported no significant difference in the distribution of stroke subtype and severity, including fatal strokes, in women receiving estrogen-alone compared to placebo. Estrogen-alone increased the risk of ischemic stroke, and this excess risk was present in all subgroups of women examined.^10 See Table 5.

Timing of initiation of estrogen-alone therapy relative to the start of menopause may affect the overall risk benefit profile. The WHI estrogen-alone substudy stratified by age showed in women 50 to 59 years of age a non-significant trend toward reduced risk for CHD [hazard ratio (HR) 0.63 (95 percent CI, 0.36-1.09)] and overall mortality [HR 0.71 (95 percent CI, 0.46-1.11)].

WHI Estrogen Plus Progestin Substudy

The WHI estrogen plus progestin substudy was stopped early. According to the predefined stopping rule, after an average follow-up of 5.6 years of treatment, the increased risk of invasive breast cancer and cardiovascular events exceeded the specified benefits included in the "global index". The absolute excess risk of events included in the “global index” was 19 per 10,000 women-years.

For those outcomes included in the WHI “global index” that reached statistical significance after 5.6 years of follow-up, the absolute excess risks per 10,000 women-years in the group treated with CE plus MPA were 7 more CHD events, 8 more strokes, 10 more PEs, and 8 more invasive breast cancers, while the absolute risk reduction per 10,000 women-years were 6 fewer colorectal cancers and 5 fewer hip fractures.

Results of the CE plus MPA substudy, which included 16,608 women (average 63 years of age, range 50 to 79; 83.9 percent White, 6.5 percent Black, 5.4 percent Hispanic, 3.9 percent Other), are presented in Table 6. These results reflect centrally adjudicated data after an average follow-up of 5.6 years.

Table 6: Relative and Absolute Risk Seen in the Estrogen Plus Progestin Substudy of WHI at an Average of 5.6 Years a,b

Event | Relative Risk CE/MPA vs. placebo; (95% nCIc) | CE/MPA n = 8,506 | Placebo; n = 8,102
Event | Relative Risk CE/MPA vs. placebo; (95% nCIc) | Absolute Risk per 10,000 Women-years
CHD events | 1.23 (0.99-1.53) | 41 | 34
Non-fatal MI | 1.28 (1.00-1.63) | 31 | 25
CHD death | 1.10 (0.70-1.75) | 8 | 8
All strokes | 1.31 (1.03-1.68) | 33 | 25
Ischemic stroke | 1.44 (1.09-1.90) | 26 | 18
Deep vein thrombosisd | 1.95 (1.43-2.67) | 26 | 13
Pulmonary embolism | 2.13 (1.45-3.11) | 18 | 8
Invasive breast cancere | 1.24 (1.01-1.54) | 41 | 33
Colorectal cancer | 0.61 (0.42-0.87) | 10 | 16
Endometrial cancerd | 0.81 (0.48-1.36) | 6 | 7
Cervical cancerd | 1.44 (0.47-4.42) | 2 | 1
Hip fracture | 0.67 (0.47-0.96) | 11 | 16
Vertebral fracturesd | 0.65 (0.46-0.92) | 11 | 17
Lower arm/wrist fracturesd | 0.71 (0.59-0.85) | 44 | 62
Total fracturesd | 0.76 (0.69-0.83) | 152 | 199
Overall mortalityf | 1.00 (0.83-1.19) | 52 | 52
Global Indexg | 1.13 (1.02-1.25) | 184 | 165

a) Adapted from numerous WHI publications. WHI publications can be viewed at www.nhlbi.nih.gov/whi.
b) Results are based on centrally adjudicated data.
c) Nominal confidence intervals unadjusted for multiple looks and multiple comparisons.
d) Not included in “global index”.
e) Includes metastatic and non-metastatic breast cancer, with the exception of in situ breast cancer.
f) All deaths, except from breast or colorectal cancer, definite or probable CHD, PE or cerebrovascular disease.
g) A subset of the events was combined in a "global index”, defined as the earliest occurrence of CHD events, invasive breast cancer, stroke, pulmonary embolism, endometrial cancer, colorectal cancer, hip fracture, or death due to other causes.

Timing of initiation of estrogen plus progestin therapy relative to the start of menopause may affect the overall risk benefit profile. The WHI estrogen plus progestin substudy stratified by age showed in women 50 to 59 years of age a non-significant trend toward reduced risk for overall mortality [HR 0.69 (95 percent CI 0.44-1.07)].

14.3 Women's Health Initiative Memory Study

The WHIMS estrogen-alone ancillary study of WHI enrolled 2,947 predominantly healthy hysterectomized postmenopausal women 65 to 79 years of age and older (45 percent were 65 to 69 years of age; 36 percent were 70 to 74 years of age; 19 percent were 75 years of age and older) to evaluate the effects of daily CE (0.625 mg)-alone on the incidence of probable dementia (primary outcome) compared to placebo.

After an average follow-up of 5.2 years, the relative risk of probable dementia for CE-alone versus placebo was 1.49 (95 percent CI, 0.83-2.66). The absolute risk of probable dementia for CE-alone versus placebo was 37 versus 25 cases per 10,000 women-years. Probable dementia as defined in the study included Alzheimer’s disease (AD), vascular dementia (VaD) and mixed types (having features of both AD and VaD). The most common classification of probable dementia in the treatment group and the placebo group was AD. Since the ancillary study was conducted in women 65 to 79 years of age, it is unknown whether these findings apply to younger postmenopausal women [see Warnings and Precautions (5.3), and Use in Specific Populations (8.5)].

The WHIMS estrogen plus progestin ancillary study enrolled 4,532 predominantly healthy postmenopausal women 65 years of age and older (47 percent were 65 to 69 years of age; 35 percent were 70 to 74 years of age; and 18 percent were 75 years of age and older) to evaluate the effects of daily CE (0.625 mg) plus MPA (2.5 mg) on the incidence of probable dementia (primary outcome) compared to placebo.

After an average follow-up of 4 years, the relative risk of probable dementia for CE plus MPA versus placebo was 2.05 (95 percent CI, 1.21-3.48). The absolute risk of probable dementia for CE plus MPA versus placebo was 45 versus 22 cases per 10,000 women-years. Probable dementia as defined in the study included AD, VaD and mixed types (having features of both AD and VaD). The most common classification of probable dementia in the treatment group and the placebo group was AD. Since the ancillary study was conducted in women 65 to 79 years of age, it is unknown whether these findings apply to younger postmenopausal women [see Warnings and Precautions (5.3), and Use in Specific Populations (8.5)].

When data from the two populations were pooled as planned in the WHIMS protocol, the reported overall relative risk for probable dementia was 1.76 (95 percent CI, 1.19-2.60). Differences between groups became apparent in the first year of treatment. It is unknown whether these findings apply to younger postmenopausal women [see Warnings and Precautions (5.3), and Use in Specific Populations (8.5)].

15 REFERENCES

1. Rossouw JE, et al. Postmenopausal Hormone Therapy and Risk of Cardiovascular Disease by Age and Years Since Menopause. JAMA. 2007;297:1465–1477.
2. Hsia J, et al. Conjugated Equine Estrogens and Coronary Heart Disease. Arch Int Med. 2006;166:357-365.
3. Curb JD, et al. Venous Thrombosis and Conjugated Equine Estrogen in Women Without a Uterus. Arch Int Med. 2006;166:772–780.
4. Cushman M, et al. Estrogen Plus Progestin and Risk of Venous Thrombosis. JAMA. 2004;292:1573–1580.
5. Stefanick ML, et al. Effects of Conjugated Equine Estrogens on Breast Cancer and Mammography Screening in Postmenopausal Women With Hysterectomy. JAMA. 2006;295:1647–1657.
6. Chlebowski RT, et al. Influence of Estrogen Plus Progestin on Breast Cancer and Mammography in Healthy Postmenopausal Women. JAMA. 2003;289:3234–3253.
7. Anderson GL, et al. Effects of Estrogen Plus Progestin on Gynecologic Cancers and Associated Diagnostic Procedures. JAMA. 2003;290:1739–1748.
8. Shumaker SA, et al. Conjugated Equine Estrogens and Incidence of Probable Dementia and Mild Cognitive Impairment in Postmenopausal Women. JAMA. 2004;291:2947–2958.
9. Jackson RD, et al. Effects of Conjugated Equine Estrogen on Risk of Fractures and BMD in Postmenopausal Women With Hysterectomy: Results From the Women's Health Initiative Randomized Trial. J Bone Miner Res. 2006;21:817–828.
10. Hendrix SL, et al. Effects of Conjugated Equine Estrogen on Stroke in the Women's Health Initiative. Circulation. 2006;113:2425–2434.

16 HOW SUPPLIED/STORAGE AND HANDLING

16.1 How Supplied

Menostar(estradiol transdermal system), 14 mcg per day — each 3.25 cm^2 system contains 1 mg of estradiol USP

Individual Carton of 4 systems NDC 50419-455-04

16.2 Storage and Handling

Store at 20°C to 25°C (68°F to 77°F); excursions permitted between 15°C and 30°C (59°F and 86°F). Do not store above 86°F (30°C).

Do not store unpouched. Apply immediately upon removal from the protective pouch.

Used transdermal systems still contain active hormone. To discard, fold the sticky side of the transdermal system together, place it in a child-proof container, and place this container in the trash. Used transdermal systems should not be flushed in the toilet.

17 PATIENT COUNSELING INFORMATION

Advise women to read the FDA-approved patient labeling (Patient Information and Instructions for Use).

Vaginal Bleeding

Inform postmenopausal women to report any vaginal bleeding to their healthcare provider as soon as possible [see Warning and Precautions (5.2)].

Possible Serious Adverse Reactions with Estrogen-Alone Therapy

Inform postmenopausal women of possible serious adverse reactions of estrogen-alone therapy including Cardiovascular Disorders, Malignant Neoplasms, and Probable Dementia [see Warnings and Precautions (5.1, 5.2, 5.3)].

Possible Common Adverse Reactions with Estrogen-Alone Therapy

Inform postmenopausal women of possible less serious but common adverse reactions of estrogen-alone therapy such as headache, breast pain and tenderness, nausea and vomiting.

Patient Package Insert

Patient Information

MENOSTAR (Mĕn-ō-stär)

(estradiol transdermal system)

Read this Patient Information before you start using MENOSTAR and each time you get a refill. There may be new information. This information does not take the place of talking to your healthcare provider about your menopausal symptoms or your treatment.

What is the most important information I should know about MENOSTAR (an estrogen hormone)?

- Using estrogen-alone may increase your chance of getting cancer of the uterus (womb).
- Report any unusual vaginal bleeding right away while you are using MENOSTAR. Vaginal bleeding after menopause may be a warning sign of cancer of the uterus (womb). Your healthcare provider should check any unusual vaginal bleeding to find out the cause.
- Do not use estrogen-alone to prevent heart disease, heart attacks, strokes, or dementia (decline in brain function).
- Using estrogen-alone may increase your chances of getting strokes or blood clots.
- Using estrogen-alone may increase your chance of getting dementia, based on a study of women age 65 years of age and older.
- Do not use estrogens with progestogens to prevent heart disease, heart attacks, strokes or dementia.
- Using estrogens with progestogens may increase your chances of getting heart attacks, strokes, breast cancer, or blood clots.
- Using estrogens with progestogens may increase your chance of getting dementia, based on a study of women age 65 years of age and older.
- Only one estrogen-alone product and dose have been shown to increase your chances of getting strokes, blood clots, and dementia. Only one estrogen with progestogen product and dose have been shown to increase your chances of getting heart attacks, strokes, breast cancer, blood clots, and dementia.
Because other products and doses have not been studied in the same way, it is not known how the use of MENOSTAR will affect your chances of these conditions. You and your healthcare provider should talk regularly about whether you still need treatment with MENOSTAR.

What is MENOSTAR?

MENOSTAR is a prescription medicine patch (transdermal system) that contains estradiol (an estrogen hormone).

What is MENOSTAR used for?

MENOSTAR is used after menopause to:

- Help reduce your chances of getting osteoporosis (thin weak bones)
Osteoporosis from menopause is a thinning of the bones that makes them weaker and easier to break. If you use MENOSTAR only to prevent osteoporosis due to menopause, talk with your healthcare provider about whether a different treatment or medicine without estrogens might be better for you.
You and your healthcare provider should talk regularly about whether you still need treatment with Menostar.

Who should not use MENOSTAR?

Do not start using MENOSTAR if you:

- have unusual vaginal bleeding
Vaginal bleeding after menopause may be a warning sign of cancer of the uterus (womb). Your healthcare provider should check any unusual vaginal bleeding to find out the cause.
- have been diagnosed with a bleeding disorder
- currently have or have had certain cancers
Estrogens may increase the chance of getting certain types of cancers, including cancer of the breast or uterus (womb). If you have or have had cancer, talk with your healthcare provider about whether you should use MENOSTAR.
- had a stroke or heart attack
- currently have or have had blood clots
- currently have or have had liver problems
- are allergic to MENOSTAR or any of the ingredients in it. See the list of ingredients in MENOSTAR at the end of this leaflet.

Before you use MENOSTAR, tell your healthcare provider about all of your medical conditions, including if you:

- have any unusual vaginal bleeding
Vaginal bleeding after menopause may be a warning sign of cancer of the uterus (womb). Your healthcare provider should check any unusual vaginal bleeding to find out the cause.
- have any other medical conditions that may become worse while you are using MENOSTAR
Your healthcare provider may need to check you more carefully if you have certain conditions, such as asthma (wheezing), epilepsy (seizures), diabetes, migraine, endometriosis, lupus, angioedema (swelling of face and tongue), or problems with your heart, liver, thyroid, kidneys, or have high calcium levels in your blood.
- are going to have surgery or will be on bed rest
Your healthcare provider will let you know if you need to stop using MENOSTAR.
- are pregnant or think you may be pregnant
MENOSTAR is not for pregnant women.
- are breastfeeding
The hormone in MENOSTAR can pass into your breast milk.

Tell your healthcare provider about all the medicines you take, including prescription and over-the-counter medicines, vitamins, and herbal supplements. Some medicines may affect how MENOSTAR works. MENOSTAR may also affect how your other medicines work. Keep a list of your medicines and show it to your healthcare provider and pharmacist when you get new medicine.

How should I use MENOSTAR?

For detailed instructions, see the step-by-step instructions for using MENOSTAR at the end of this Patient Information.

- Use MENOSTAR exactly as your healthcare provider tells you to use it.
- MENOSTAR is for skin use only.
- Change your MENOSTAR patch 1 time each week or every 7 days.
- Apply your MENOSTAR patch to a clean, dry area on your lower abdomen or buttocks. This area must be clean, dry, and free of powder, oil or lotion for your patch to stick to your skin.
- Apply your MENOSTAR patch to a different area of your abdomen or your buttocks each time. Do not use the same application site 2 times in the same week.
- Do not apply MENOSTAR to your breasts.
- If you forget to apply a new MENOSTAR patch, apply a new patch as soon as possible.
- You and your healthcare provider should talk regularly (every 3 to 6 months) about the dose you are using and whether you still need treatment with MENOSTAR.

How to Change MENOSTAR.

- When changing MENOSTAR, peel off the used patch slowly from the skin.
- After removal of MENOSTAR if any adhesive residue remains on your skin, allow the area to dry for 15 minutes. Then, gently rub the area with an oil-based cream or lotion to remove the adhesive from your skin.
- Applythe new patch to a different area of your abdomen or buttocks. This area must be clean, dry, and free of powder, oil or lotion. Do not use the same site again for at least 1 week after removal of an old patch.

What are the possible side effects of MENOSTAR?

Side effects are grouped by how serious they are and how often they happen when you are treated.

Serious, but less common side effects include:

- heart attack
- stroke
- blood clots
- breast cancer
- cancer of the lining of the uterus (womb)
- cancer of the ovary
- dementia
- high or low blood calcium
- gallbladder disease
- visual abnormalities
- high blood pressure

- high levels of fat (triglyceride) in your blood
- liver problems
- changes in your thyroid hormone levels
- fluid retention
- cancer changes of endometriosis
- enlargement of benign tumors of the uterus (“fibroids”)
- worsening of swelling of face and tongue (angioedema) in women with a history of angioedema

Call your healthcare provider right away if you get any of the following warning signs or any other unusual symptoms that concern you:

- new breast lumps
- unusual vaginal bleeding
- changes in vision or speech
- sudden new severe headaches
- severe pains in your chest or legs with or without shortness of breath, weakness and fatigue

Common side effects include:

- headache
- breast tenderness or pain
- irregular vaginal bleeding or spotting
- stomach or abdominal cramps, bloating
- nausea and vomiting

- hair loss
- fluid retention
- vaginal yeast infection
- redness and/or irritation at the patch placement site

These are not all the possible side effects of MENOSTAR. For more information, ask your healthcare provider or pharmacist. Tell your healthcare provider if you have any side effects that bother you or do not go away.

You may report side effects to FDA at 1-800-FDA-1088. You may report side effects to Bayer Healthcare Pharmaceuticals at 1-888-842-2937.

What can I do to lower my chances of a serious side effect with MENOSTAR?

- Talk with your healthcare provider regularly about whether you should continue using MENOSTAR.
- If you have a uterus, talk with your healthcare provider about whether MENOSTAR is right for you. In general, the addition of a progestogen is generally recommended for a woman with a uterus to reduce the chance of getting cancer of the uterus (womb).
- See your healthcare provider right away if you get vaginal bleeding while using MENOSTAR.
- Have a pelvic exam, breast exam and mammogram (breast X-ray) every year unless your healthcare provider tells you something else.
If members of your family have had breast cancer or if you have ever had breast lumps or an abnormal mammogram, you may need to have breast exams more often.
- If you have high blood pressure, high cholesterol (fat in the blood), diabetes, are overweight, or if you use tobacco, you may have higher chances of getting heart disease. Ask your healthcare provider for ways to lower your chances of getting heart disease.

How should I store and throw away used MENOSTAR?

- Store MENOSTAR at room temperature 68°F to 77°F (20°C to 25°C).
- Do not store MENOSTAR patches outside of their pouches. Apply immediately upon removal from the protective pouch.
- Used patches still contain estrogen. To throw away the patch, fold the sticky side of the patch together, place it in a sturdy child-proof container, and place this container in the trash. Used patches should not be flushed in the toilet.

Keep MENOSTAR and all medicines out of the reach of children.

General information about the safe and effective use of MENOSTAR.

Medicines are sometimes prescribed for conditions that are not mentioned in Patient Information leaflets. Do not use MENOSTAR for conditions for which it was not prescribed. Do not give MENOSTAR to other people, even if they have the same symptoms you have. It may harm them.

You can ask your healthcare provider or pharmacist for information about MENOSTAR that is written for health professionals. For more information, go to www.menostar-us.com or call Bayer Healthcare Pharmaceuticals Inc. at 1-888-842-2937.

What are the ingredients in MENOSTAR?

Active ingredient: estradiol

Inactive ingredients: acrylate copolymer adhesive, fatty acid esters, and polyethylene backing.

Instructions for Use

MENOSTAR (Mĕn-ō-stär)

(estradiol transdermal system)

Read this Patient Information before you start using MENOSTAR and each time you get a refill. There may be new information. This information does not take the place of talking to your healthcare provider about your menopausal symptoms or your treatment.

You will need the following supplies: See Figure A

Figure A

Step 1: Pick the days you will change your MENOSTAR.

- You will need to change your patch 1 time each week or every 7 days.

Step 2. Remove the MENOSTAR patch from the pouch.

- Remove the patch from its protective pouch by tearing at the notch (do not use scissors). See Figure B
- Do not remove your patch from the protective pouch until you are ready to apply it.

Figure B

Step 3. Remove the adhesive liner. See Figure C

- You will see that MENOSTAR is an oval shaped clear patch that is attached to a thick, hard-plastic adhesive liner and covered by a clear, plastic film. See Figure C
- To apply your patch you must first remove the protective, clear plastic film that is attached to the clear thicker plastic backing. See Figure D
- There is a silver foil-sticker attached to the inside of the pouch. Do not remove the silver foil sticker from the pouch. See Figure E

Figure C

Figure D

Figure E

Step 4. Placing the patch on your skin.

- Apply the sticky side of the patch to 1 of the areas of skin shown below. See Figure F and Figure G
- Do not touch the sticky side of the patch with your fingers.

Figure F

Figure G

Note:

- Avoid the waistline, since clothing and belts may cause the patch to be rubbed off.
- Do not apply MENOSTAR to your breasts.
- Only apply MENOSTAR to skin that is clean, dry, and free of any powder, oil, or lotion.
- Do not apply the patch to injured, burned, or irritated skin, or areas with skin conditions (such as birth marks, tattoos, or that is very hairy).

Step 5. Press the patch firmly onto your skin.

- Press the patch firmly in place with your fingers for at least 10 seconds.
- Rub the edges of the patch to make sure that it will stick to your skin. (See Figure H)

Figure H

Note:

- Contact with water while you are swimming, using a sauna, bathing, or showering may cause the patch to fall off.
- If your patch falls off reapply it. If you cannot reapply the patch, apply a new patch to another area (See Figure F and Figure G) and continue to follow your original application schedule.
- If you stop using your MENOSTAR patch or forget to apply a new patch as scheduled, you may have spotting, or bleeding, or your symptoms may come back.

Step 6: Throwing away your used patch.

- When it is time to change your patch, remove the old patch before you apply a new patch.
- To throw away the patch, fold the sticky side of the patch together, place it in a sturdy child-proof container, and place this container in the trash. Used patches should not be flushed in the toilet.

This Patient Information and Instructions for Use have been approved by the U.S Food and Drug

Administration.

Revised: 9/2021

© 2013, Bayer HealthCare Pharmaceuticals Inc. All rights reserved.

Manufactured for Bayer HealthCare Pharmaceuticals Inc.
Whippany, NJ 07981

PACKAGE/LABEL PRINCIPAL DISPLAY PANEL

Menostar Individual Carton

NDC 50419-455-04 4 Transdermal Systems

Menostar

(estradiol transdermal system)
14 mcg/day

Contents: Each 3.25 cm^2 system contains 1 mg estradiol
USP to provide 14 mcg of estradiol per day. The inactive
components are acrylate copolymer adhesive, fatty acid
esters, and polyethylene backing.

For Transdermal Use Only.

Keep this and all drugs out of the reach of children.

Rx Only